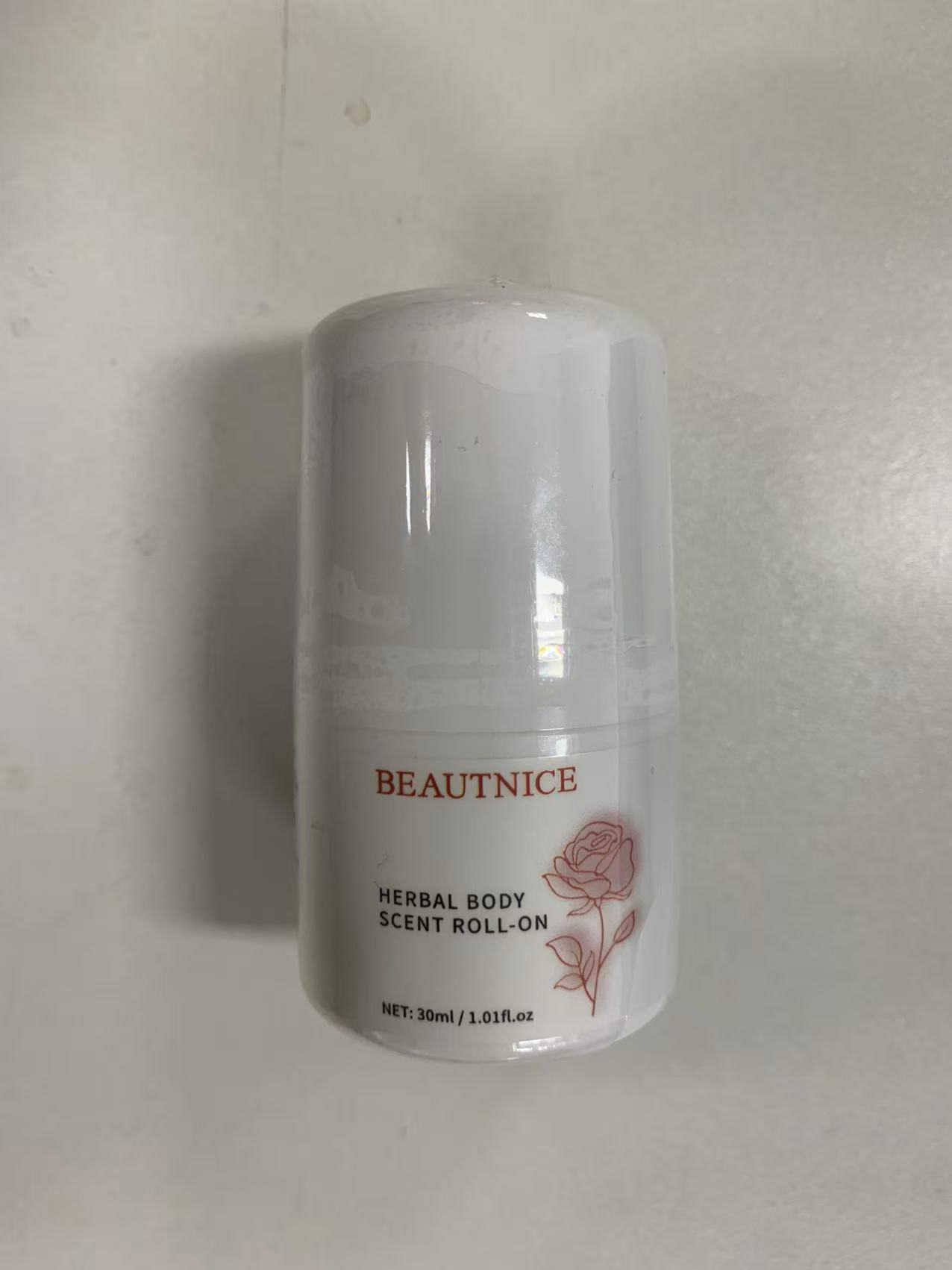 DRUG LABEL: BEAUTNICE
NDC: 85772-0004 | Form: LOTION
Manufacturer: Guangzhou Oupeng Cosmetics Co., Ltd.
Category: otc | Type: HUMAN OTC DRUG LABEL
Date: 20250626

ACTIVE INGREDIENTS: ALUMINUM CHLOROHYDRATE 10 g/100 g
INACTIVE INGREDIENTS: AQUA 67.863 g/100 g; MINERAL OIL 3.5 g/100 g; GLYCERIN 4.2 g/100 g; POLYSORBATE 60 0.4025 g/100 g; GLYCERYL STEARATE SE 1.1 g/100 g; PHENOXYETHANOL 0.3 g/100 g; CARBOMER 0.28 g/100 g; METHYLPARABEN 0.12 g/100 g; TRIETHANOLAMINE 0.285 g/100 g; PEG/PPG-17/6 COPOLYMER 1.2 g/100 g; NIACINAMIDE 2.005 g/100 g; GLYCYRRHIZA INFLATA ROOT 0.123 g/100 g; 1,2-HEXANEDIOL 0.7 g/100 g; HYDROXYACETOPHENONE 0.25 g/100 g; SODIUM HYALURONATE 0.121 g/100 g; SCUTELLARIA BAICALENSIS ROOT 0.15 g/100 g; SOPHORA FLAVESCENS ROOT 0.1 g/100 g; ALCEA ROSEA SEED 0.03 g/100 g; FOLIC ACID 0.04 g/100 g; BUTYLENE GLYCOL 3.055 g/100 g; SOYBEAN 0.222 g/100 g; SORBITAN STEARATE 0.605 g/100 g; TRILAURETH-4 PHOSPHATE 0.45 g/100 g; FRAGRANCE 13576 0.081 g/100 g; HYDROXYETHYLCELLULOSE 0.3525 g/100 g; ALCEA ROSEA FLOWER 0.0605 g/100 g; ETHYLHEXYLGLYCERIN 0.1515 g/100 g; PEG-100 STEARATE 2.253 g/100 g

Active ingredient(s)

Aluminum Chlorohydrate 10 %

Purpose(s)

Antiperspirant

Uses

Reduces underarm wetness

Warnings

For external use only.

Do not use

On broken skin

Ask a doctor before use if you have

Kidney disease

When using this product

Do not get into eyes. If product gets into eyes, rinse thoroughly with water.

Stop use and ask a doctor if

Rash or irritation occurs

Pregnancy or breast feeding section

If pregnant or breast-feeding, ask a health professional before use.

Keep out of reach of children

If swallowed, get medical help or contact a Poison Control Center right away.

Directions

- Apply to underarms only
- Apply after cleansing and drying your skin

Other information

- Store in a cool, dry place away from direct sunlight.

Inactive ingredients

AQUA, MINERAL OIL, GLYCERIN, GLYCERYL STEARATE, PEG-100 STEARATE, SORBITAN STEARATE, POLYSORBATE 60, GLYCERYL STEARATES, PHENOXYETHANOL, TRILAURETH-4 PHOSPHATE, FRAGRANCE, CARBOMER, METHYLPARABEN, TRIETHANOLAMINE, HYDROXYETHYLCELLULOSE, PEG/PPG-17/6 COPOLYMER, NIACINAMIDE, BIFIDA FERMENT LYSATE, BUTYLENE GLYCOL, SCUTELLARIA BAICALENSIS ROOT EXTRACT, GLYCYRRHIZA INFLATA ROOT EXTRACT, SOPHORA FLAVESCENS ROOT EXTRACT, ROSE EXTRACT, ROSE FLOWER OIL, 1,2-HEXANEDIOL, HYDROXYACETOPHENONE, BACILLUS/SOYBEAN FERMENT EXTRACT, FOLIC ACID, ETHYLHEXYLGLYCERIN, SODIUM HYALURONATE

Questions or comments?

934-935-7135 / Yiqinzhi726@gmail.com

Box Front Panel

BEAUTNICE

HERBAL BODY SCENT ROLL-ON

NET: 30ml / 1.01fl.oz